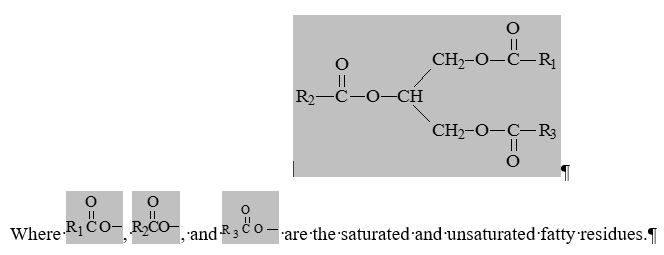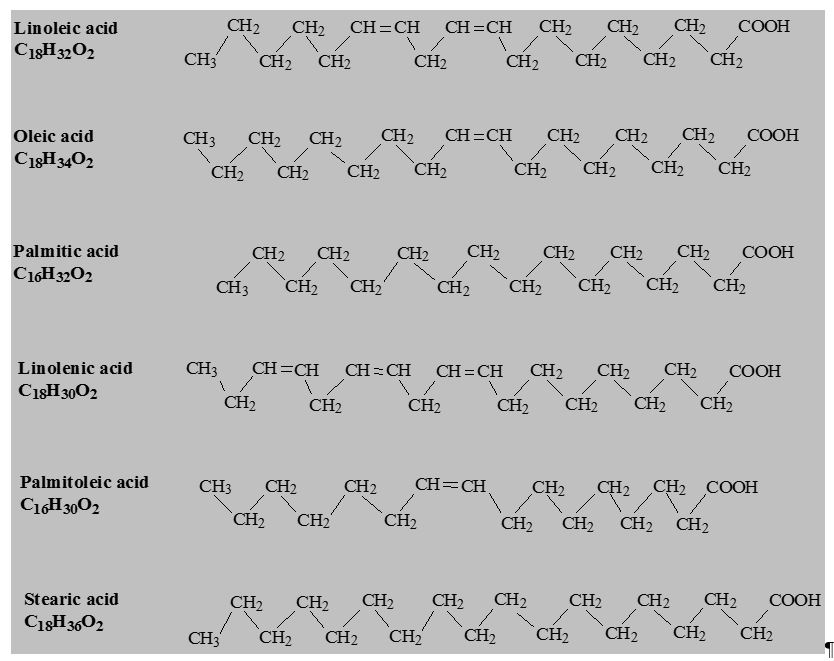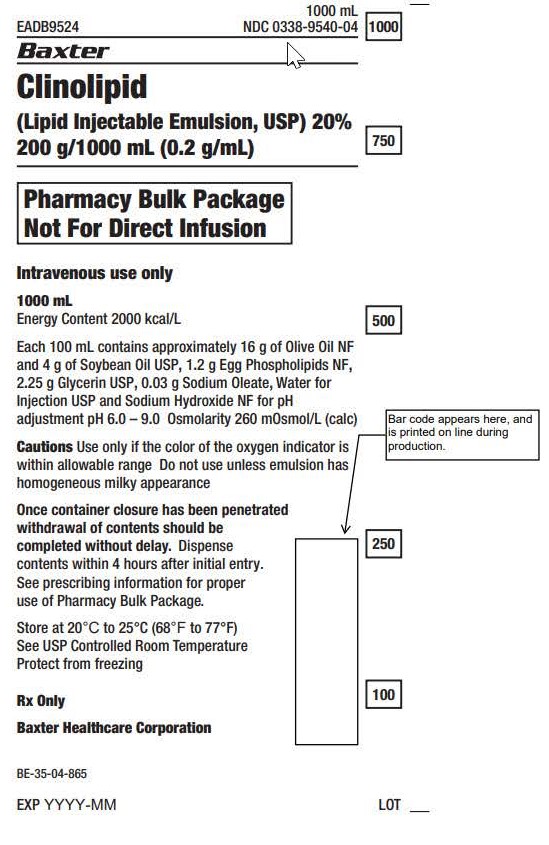 DRUG LABEL: Clinolipid
NDC: 0338-9540 | Form: INJECTION, EMULSION
Manufacturer: Baxter Healthcare Corporation
Category: prescription | Type: HUMAN PRESCRIPTION DRUG LABEL
Date: 20250724

ACTIVE INGREDIENTS: OLIVE OIL 16 g/100 mL; SOYBEAN OIL 4 g/100 mL
INACTIVE INGREDIENTS: EGG PHOSPHOLIPIDS 1.20 g/100 mL; GLYCERIN 2.25 g/100 mL; SODIUM OLEATE 0.03 g/100 mL

HIGHLIGHTS OF PRESCRIBING INFORMATION

These highlights do not include all the information needed to use CLINOLIPID safely and effectively. See full prescribing information for CLINOLIPID.
CLINOLIPID (lipid injectable emulsion), for intravenous use
Initial U.S. Approval: 1975

RECENT MAJOR CHANGES

Warnings and Precautions (5.3) 7/2025

1 INDICATIONS AND USAGE

CLINOLIPID is indicated in adults and pediatric patients, including term and preterm neonates, as a source of calories and essential fatty acids for parenteral nutrition (PN) when oral or enteral nutrition is not possible, insufficient, or contraindicated. (1)

2 DOSAGE AND ADMINISTRATION

- Use a 1.2 micron in-line filter when administering to a patient. (2.1)
- For infusion into a central or peripheral vein. (2.2)
- See full prescribing information for administration and admixing instructions. (2.2, 2.3)
- CLINOLIPID Pharmacy Bulk Package is only indicated for use in pharmacy admixture programs for the preparation of three-in-one or total nutrition admixtures. (2.2)
- Protect the admixed parenteral solution from light. (2.3)
- Recommended dosage depends on age, energy expenditure, clinical status, body weight, tolerance, ability to metabolize and eliminate lipids, and consideration of additional energy given to the patient. (2.4)
- For information on the age-appropriate infusion rate, see the full prescribing information. (2.4, 5.1)

Age | Initial Dose | Maximum Dose
Birth to 2 years of age (including preterm and term neonates) | 0.5 to 1 g/kg/day | 3 g/kg/day
Pediatric patients; 2 to less than 12 years of age | 1 to 2 g/kg/day | 3 g/kg/day
Pediatric patients 12 to 17 years of age | 1 g/kg/day | 3 g/kg/day
Adults | 1 to 1.5 g/kg/day | 2.5 g/kg/day

3 DOSAGE FORMS AND STRENGTHS

Injectable emulsion:

- 20% (20 g/100 mL) (0.2 g/mL) of lipid in 100 mL single-dose flexible container (3)
- 20% (50 g/250 mL) (0.2 g/mL) of lipid in 250 mL single-dose flexible container (3)
- 20% (100 g/500 mL) (0.2 g/mL) of lipid in 500 mL single-dose flexible container (3)
- 20% (200 g/1,000 mL) (0.2 g/mL) of lipid in 1,000 mL Pharmacy Bulk Package (3)

4 CONTRAINDICATIONS

- Known hypersensitivity to egg, soybean, peanut, or any of the active or inactive ingredients. (4)
- Severe disorders of lipid metabolism characterized by
  hypertriglyceridemia (serum triglycerides >1,000 mg/dL). (4, 5.7)

5 WARNINGS AND PRECAUTIONS

- Clinical Decompensation with Rapid Infusion of Intravenous Lipid Emulsion in Neonates and Infants: Acute respiratory distress, metabolic acidosis, and death after rapid infusion of intravenous lipid emulsions have been reported. (5.1, 8.4)
- Parenteral Nutrition-Associated Liver Disease: Increased risk in patients who receive parenteral nutrition for greater than 2 weeks, especially preterm neonates. Monitor liver tests: if abnormalities occur, consider discontinuation or dosage reduction. (5.2, 8.4)
- Hypersensitivity Reactions: Monitor for signs or symptoms. Discontinue infusion if reactions occur. (5.3)
- Risk of Infections, Fat Overload Syndrome, Refeeding Syndrome, Hypertriglyceridemia, and Essential Fatty Acid Deficiency: Monitor for signs and symptoms; monitor laboratory parameters. (5.4, 5.5, 5.6, 5.7, 5.9)
- Aluminum Toxicity: Increased risk in patients with renal impairment, including preterm neonates. (5.8, 8.4)

6 ADVERSE REACTIONS

Most common (≥5%) adverse drug reactions from clinical trials in adults were nausea and vomiting, hyperlipidemia, hyperglycemia, hypoproteinemia, and abnormal liver function tests. Most common (≥5%) adverse reactions from clinical trials in pediatric patients were hyperbilirubinemia, patent ductus arteriosus, anemia, gastroesophageal reflux disease, bradycardia, feeding intolerance, neonatal intraventricular hemorrhage, increased alkaline phosphatase, atrial septal defect, hyponatremia, sepsis, and infantile apnea. (6.1)

To report SUSPECTED ADVERSE REACTIONS, contact Baxter Healthcare at 1-866-888-2472 or FDA at 1-800-FDA-1088 or www.fda.gov/medwatch.

7 DRUG INTERACTIONS

The anticoagulant activity of coumarin derivatives, including warfarin, may be counteracted. (7)

FULL PRESCRIBING INFORMATION

1 INDICATIONS AND USAGE

CLINOLIPID is indicated in adults and pediatric patients, including term and preterm neonates, as a source of calories and essential fatty acids for parenteral nutrition (PN) when oral or enteral nutrition is not possible, insufficient, or contraindicated.

2 DOSAGE AND ADMINISTRATION

2.1 Use of an Inline Filter When Administering CLINOLIPID to a Patient

Fragments of the administration port membrane could be dislodged into the bag after spiking. Use a 1.2 micron in-line filter during administration of CLINOLIPID (alone or as part of an admixture) to remove particulate matter or micro-precipitate contamination during administration of a lipid injection (alone or as part of an admixture). Particulate matter greater than 5 microns has the capability of obstructing blood flow through capillaries, which could lead to embolism and vascular occlusion. Do not use filters of less than 1.2 micron pore size with lipid emulsions.

2.2 Important Administration Instructions

Before opening the overwrap, check the color of the oxygen indicator. Compare the color of the indicator to the reference color printed next to the OK symbol depicted in the printed area of the indicator label. Do not use the product if the color of the oxygen absorber/indicator does not correspond to the reference color printed next to the OK symbol.

After opening the bag, use the contents immediately and discard unused portion.

Visually inspect that the emulsion is a homogeneous liquid with a milky appearance. Inspect for particulate matter and discoloration prior to administration, whenever solution and container permit.

Do not exceed the recommended maximum infusion rate (0.75 mL/kg/hour for pediatric patients and 0.5 mL/kg/hour for adults) [see Dosage and Administration (2.4) and Warnings and Precautions (5.1)].

When Administering CLINOLIPID to a Patient:

Do not connect flexible bags in series to avoid air embolism due to possible residual gas contained in the primary bag.

Air embolism can result if residual gas in the bag is not fully evacuated prior to administration if the flexible bag is pressurized to increase flow rates.

Do not use vented administration sets with the vent in the open position. This can result in air embolism.

If CLINOLIPID is mixed with dextrose and/or amino acid solutions, check the compatibility before administration by inspecting the mixture closely for the presence of precipitates. Formation of precipitates could result in vascular occlusion.

CLINOLIPID can be administered via central or peripheral vein. When administered with dextrose and amino acids, the choice of a central or peripheral venous route should depend on the osmolarity of the final infusate.

Do not use administration sets and lines that contain di-2-ethylhexyl phthalate (DEHP).

Use only a 1.2 micron pore size in-line filter to administer CLINOLIPID. DO NOT use any size less than 1.2 micron pore size in-line filter [see Dosage and Administration (2.1)].

CLINOLIPID 100 mL, 250 mL and 500 mL single-dose Flexible Containers:

- After removing the overpouch, infuse immediately. If not used immediately, the product should be stored for no longer than 24 hours at no more than 25°C (77°F).

CLINOLIPID 1,000 mL Pharmacy Bulk Package:

- For admixing use only and not for direct intravenous infusion. Prior to administration, transfer to a separate PN container for individual patient use.
- Transfer the contents through the infusion port using a suitable sterile transfer device or dispensing set. Discard any unused contents. Discard any unused portion.
- Use the Pharmacy Bulk Package immediately for admixing after removal from overpouch. If not used immediately, the product should be stored for no longer than 24 hours at no more than 25°C (77°F).
- Once the closure is penetrated use Pharmacy Bulk Package contents within 4 hours.

2.3 Admixing Guidelines

When Admixing CLINOLIPID in the Pharmacy:

Prepare the admixture using strict aseptic techniques to avoid microbial contamination.

Do not add additives directly to CLINOLIPID. Do not add CLINOLIPID to the total parenteral nutrition container first; destabilization of the lipid may occur from such an admixture.

Do not use the EXACTAMIX Inlet REF 173 (H938173) with an EXACTAMIX compounder to transfer CLINOLIPID. This inlet spike has been associated with dislodgement of the administration port membrane into the CLINOLIPID bag. Use of EXACTAMIX Inlet REF 174 (H938174) is recommended.

The following proper mixing sequence must be followed to minimize pH related problems by ensuring that typically acidic Dextrose Injections are not mixed with lipid emulsions alone:

1. Transfer Dextrose Injection to the Total Parenteral Nutrition Admixture Container
2. Transfer Amino Acid Injection
3. Transfer Lipid Emulsion

Amino Acid Injection, Dextrose Injection and Lipid Emulsions may be simultaneously transferred to the admixture container. Use gentle agitation during admixing to minimize localized concentration effects; shake bags gently after each addition.

The prime destabilizers of emulsions are excessive acidity (such as a pH below 5) and inappropriate electrolyte content. Give careful consideration to additions of divalent cations (Ca^++ and Mg^++), which have been shown to cause emulsion instability. Amino acid solutions exert buffering effects that protect the emulsion.

Inspect the admixture closely for separation of the emulsion. This can be visibly identified by a yellowish streaking or the accumulation of yellowish droplets in the admixed emulsion. The admixture should also be examined for particulates. Discard the admixture if any of the above is observed.

Protect the admixed parenteral nutrition solution from light.

2.4 Dosing Considerations

The recommended nutritional requirements of lipid and recommended dosages of CLINOLIPID to be administered to meet those requirements for pediatric and adult patients are provided in Table 1, along with recommendations for the initial and maximum infusion rates. For complete parenteral nutrition, concomitant supplementation with amino acids, carbohydrates, electrolytes, vitamins, and trace elements is necessary.

Prior to administration of CLINOLIPID, correct severe water and electrolyte disorders, severe fluid overload states, and severe metabolic disorders. Before starting the infusion, obtain serum triglyceride levels to establish the baseline value. In patients with elevated triglyceride levels, initiate CLINOLIPID injection at a lower dose, and advance in smaller increments, checking the triglyceride levels prior to each adjustment.

Adjust the infusion rate by taking into account the dose being administered, the daily volume intake, and the duration of the infusion. Do not exceed the maximum infusion rates in Table 1 [see Warnings and Precautions (5.1) and see Overdosage (10)].

The recommended duration of infusion for a parenteral nutrition bag is between 12 and 24 hours, depending on the clinical situation. For preterm and term neonates, the recommended duration of infusion is 20 to 24 hours. Treatment with parenteral nutrition may be continued for as long as required by the patient’s condition.

The maximum daily dosage of CLINOLIPID should be based on individual total nutritional requirements and patient tolerance (Error! Hyperlink reference not valid.).

Table 1: Recommended Pediatric and Adult Dosage and Infusion Rate
Age | Nutritional Requirements | Direct Infusion Rate [CLINOLIPID Pharmacy Bulk Package is not intended for direct intravenous administration.]
Age | Recommended Initial Dosage and Maximum Dosage | Initial | Maximum
Birth to 2 years of age (including preterm and term neonates [The neonatal period is defined as including term, post-term, and preterm newborn infants. The neonatal period for term and post-term infants is the day of birth plus 27 days. For preterm infants, the neonatal period is defined as the day of birth through the expected age of delivery plus 27 days (i.e., 44 weeks post-menstrual age).]) [see Warnings and Precautions (5.1)] | Initial 0.5 to 1g/kg/day not to exceed 3 g/kg/day [Daily dosage should also not exceed a maximum of 60% of total energy requirements [see Overdosage (10)].] | 0.1 to 0.2 mL/kg/hour for the first 15 to 30 minutes; gradually increase the required rate after 30 minutes | 0.75 mL/kg/hour
Pediatric patients 2 to less than 12 years of age | Initial 1 to 2 g/kg/day not to exceed 3 g/kg/day | 0.2 to 0.4 mL/kg/hour for the first 15 to 30 minutes; gradually increase the required rate after 30 minutes | 0.75 mL/kg/hour
Pediatric patients 12 to 17 years of age | Initial 1 g/kg/day not to exceed 3 g/kg/day | 0.2 to 0.4 mL/kg/hour for the first 15 to 30 minutes; gradually increase the required rate after 30 minutes | 0.75 mL/kg/hour
Adults | 1 to 1.5 g/kg/day not to exceed 2.5 g/kg/day | 0.2 mL/kg/hour for the first 15 to 30 minutes; if tolerated, gradually increase the required rate after 30 minutes | 0.5 mL/kg/hour

3 DOSAGE FORMS AND STRENGTHS

CLINOLIPID is a sterile, homogenous, white, milky, lipid injectable emulsion supplied as:

- 20% (20 g/100 mL)(0.2g/mL) of lipid in 100 mL single-dose Flexible Container
- 20% (50 g/250 mL)(0.2g/mL) of lipid in 250 mL single-dose Flexible Container
- 20% (100 g/500 mL)(0.2g/mL) of lipid in 500 mL single-dose Flexible Container
- 20% (200 g/1,000 mL)(0.2g/mL) of lipid in 1,000 mL Pharmacy Bulk Package

4 CONTRAINDICATIONS

The use of CLINOLIPID is contraindicated in patients with the following:

- Known hypersensitivity to egg, soybean, peanut or to any of the active or inactive ingredients in CLINOLIPID [see Warnings and Precautions (5.3)].
- Severe disorders of lipid metabolism characterized by hypertriglyceridemia (serum triglyceride >1,000 mg/dL) [see Warnings and Precautions (5.7)].

5 WARNINGS AND PRECAUTIONS

5.1 Clinical Decompensation with Rapid Infusion of Intravenous Lipid Emulsion in Neonates and Infants

In the postmarketing setting, serious adverse reactions including acute respiratory distress, metabolic acidosis, and death have been reported in neonates and infants after rapid infusion of intravenous lipid emulsions. Hypertriglyceridemia was commonly reported.

Strictly adhere to the recommended total daily dosage; the hourly infusion rate should not exceed 0.75 mL/kg/hour [see Dosage and Administration (2.4)].

Preterm and small for gestational age infants have poor clearance of intravenous lipid emulsion and increased free fatty acid plasma levels following lipid emulsion infusion. The risk due to poor lipid clearance should be considered when administering intravenous lipid emulsions.

Carefully monitor the infant’s ability to eliminate the infused lipids from the circulation (e.g., measure serum triglycerides and/or plasma free fatty acid levels). If signs of poor clearance of lipids from the circulation occur, stop the infusion and initiate a medical evaluation [see Warnings and Precautions (5.5, 5.7) and Overdosage (10)].

5.2 Parenteral Nutrition Associated Liver Disease and Other Hepatobiliary Disorders

Risk of Parenteral Nutrition-Associated Liver Disease

Parenteral nutrition-associated liver disease (PNALD), also referred to as intestinal failure-associated liver disease (IFALD), can present as cholestasis or hepatic steatosis, and may progress to steatohepatitis with fibrosis and cirrhosis (possibly leading to chronic hepatic failure). The etiology of PNALD is multifactorial; however, intravenously administered phytosterols (plant sterols) contained in plant-derived lipid emulsions, including CLINOLIPID, have been associated with development of PNALD.

Monitor liver tests in patients treated with CLINOLIPID and consider discontinuation or dosage reduction if abnormalities occur.

Other Hepatobiliary Disorders

Hepatobiliary disorders including cholecystitis and cholelithiasis have developed in some PN-treated patients without preexisting liver disease.

Monitor liver tests when administering CLINOLIPID. Patients developing signs of hepatobiliary disorders should be assessed early to determine whether these conditions are related to CLINOLIPID use.

5.3 Hypersensitivity Reactions

CLINOLIPID contains soybean oil and egg phospholipids, which may cause hypersensitivity reactions. Cross reactions have been observed between soybean and peanut. In postmarketing experience, anaphylaxis has been reported following CLINOLIPID administration [see Adverse Reactions (6.2)].

CLINOLIPID is contraindicated in patients with known hypersensitivity to egg, soybean, peanut, or any of the active or inactive ingredients in CLINOLIPID [see Contraindications (4)]. If a hypersensitivity reaction occurs, stop infusion of CLINOLIPID immediately and initiate appropriate treatment and supportive measures.

5.4 Infections

Lipid emulsions, such as CLINOLIPID, can support microbial growth and are an independent risk factor for the development of catheter-related bloodstream infections. To decrease the risk of infectious complications, ensure aseptic techniques are used for catheter placement, catheter maintenance, and preparation and administration of CLINOLIPID.

Monitor for signs and symptoms of infection including fever and chills, as well as laboratory test results that might indicate infection (including leukocytosis and hyperglycemia). Perform frequent checks of the intravenous catheter insertion site for edema, redness, and discharge.

5.5 Fat Overload Syndrome

Fat overload syndrome is a rare condition that has been reported with intravenous lipid formulations and is characterized by a sudden deterioration in the patient's condition (e.g., fever, anemia, leukopenia, thrombocytopenia, coagulation disorders, hyperlipidemia, hepatomegaly, deteriorating liver function, and central nervous system manifestations such as coma). A reduced or limited ability to metabolize lipids, accompanied by prolonged plasma clearance (resulting in higher lipid levels), may result in this syndrome. Although fat overload syndrome has been most frequently observed when the recommended lipid dose or infusion rate was exceeded, cases have also been described when the lipid formulation was administered according to instructions.

If signs or symptoms of fat overload syndrome occur, stop CLINOLIPID. The syndrome is usually reversible when the infusion of the lipid emulsion is stopped.

5.6 Refeeding Syndrome

Administering PN to severely undernourished patients may result in the refeeding syndrome, which is characterized by intracellular shift of potassium, phosphorus, and magnesium as the patients become anabolic. Thiamine deficiency and fluid retention may also develop. To prevent these complications, closely monitor severely malnourished patients and slowly increase their nutrient intake.

5.7 Hypertriglyceridemia

The use of CLINOLIPID is contraindicated in patients with hypertriglyceridemia with serum triglyceride concentrations >1,000 mg/dL.

Patients with conditions such as inherited lipid disorders, obesity, diabetes mellitus, or metabolic syndromes have a higher risk of developing hypertriglyceridemia with the use of CLINOLIPID. In addition, patients with hypertriglyceridemia may have worsening of their hypertriglyceridemia with administration of CLINOLIPID. Excessive dextrose administration may further increase such risk.

Evaluate patients’ capacity to metabolize and eliminate the infused lipid emulsion by measuring serum triglycerides before the start of infusion (baseline value) and regularly throughout treatment. If triglyceride levels are above 400 mg/dL in adults, stop the CLINOLIPID infusion and monitor serum triglyceride levels to avoid clinical consequences of hypertriglyceridemia such as pancreatitis.

To minimize the risk of new or worsening of hypertriglyceridemia, assess high-risk patients for their overall energy intake including other sources of lipids and dextrose, as well as concomitant drugs that may affect lipid and dextrose metabolism.

5.8 Aluminum Toxicity

CLINOLIPID contains no more than 25 mcg/L of aluminum.

The aluminum contained in CLINOLIPID may reach toxic levels with prolonged administration in patients with impaired kidney function. Preterm infants are at greater risk because their kidneys are immature, and they require large amounts of calcium and phosphate solutions that contain aluminum.

Patients with impaired kidney function, including preterm infants, who receive parenteral levels of aluminum at greater than 4 to 5 mcg/kg/day, accumulate aluminum at levels associated with central nervous system and bone toxicity. Tissue loading may occur at even lower rates of administration of total parenteral nutrition products.

5.9 Essential Fatty Acid Deficiency

In pediatric trials, EFAD was defined by calculating the Holman index (the triene [Mead acid] to tetraene [arachidonic acid] ratio; T:T ratio > 0.4). One patient treated with CLINOLIPID became at risk for EFAD (T:T ratio >0.2) after 14 days of treatment. No cases of biochemical EFAD and no cases of clinical EFAD were observed; however, the median treatment duration in three of the four pediatric trials was 15 days or less. There are insufficient data to determine whether CLINOLIPID can supply adequate amounts of essential fatty acids in patients who may need treatment for more than 15 days.

Monitor patients for laboratory evidence (e.g., abnormal fatty acid levels) and clinical symptoms of EFAD (e.g., skin manifestations, poor growth). Laboratory testing using the triene to tetraene ratio may not be adequate to diagnose EFAD, and assessment of individual fatty acid levels may be needed. Ensure patients are receiving recommended dosages of CLINOLIPID to prevent EFAD [see Dosage and Administration (2.4) and Description (11)].

5.10 Monitoring/Laboratory Tests

Routine Monitoring

Monitor fluid status closely in patients with pulmonary edema or heart failure.

Throughout treatment, monitor serum triglycerides [see Warnings and Precautions (5.7)], fluid and electrolyte status, serum osmolarity, blood glucose, liver and kidney function, blood count (including platelets), and coagulation parameters.

The lipids contained in CLINOLIPID may interfere with the results of some laboratory tests (e.g., hemoglobin, lactate dehydrogenase, bilirubin, oxygen saturation) if the blood is sampled before the lipids have cleared from the bloodstream. Conduct these tests at least 6 hours after stopping the infusion.

CLINOLIPID 20% contains Vitamin K that may counteract anticoagulant activity [see Drug Interactions (7)].

6 ADVERSE REACTIONS

The following clinically significant adverse reactions are described elsewhere in the labeling:

- Clinical Decompensation with Rapid Infusion of Intravenous Lipid Emulsion in Neonates and Infants [see Warnings and Precautions (5.1)]
- Parenteral Nutrition-Associated Liver Disease and Other Hepatobiliary Disorders [see Warnings and Precautions (5.2)]
- Hypersensitivity reactions [see Warnings and Precautions (5.3)]
- Infections [see Warnings and Precautions (5.4)]
- Fat overload syndrome [see Warnings and Precautions (5.5)]
- Refeeding syndrome [see Warnings and Precautions (5.6)]
- Hypertriglyceridemia [see Warnings and Precautions (5.7)]
- Aluminum toxicity [see Warnings and Precautions (5.8)]
- Essential Fatty Acid Deficiency [see Warnings and Precautions (5.9)]

6.1 Clinical Trials Experience

Because clinical trials are conducted under widely varying conditions, adverse reaction rates observed in the clinical trials of a drug cannot be directly compared to rates in the clinical trials of another drug and may not reflect the rates observed in practice.

The CLINOLIPID trials had small sample sizes and patients had a variety of underlying medical conditions both between different trials and within the individual trials. Patients had gastrointestinal diseases/dysfunction or were recovering from gastrointestinal or other surgeries, trauma, burns, or were afflicted by other chronic illness.

Adult Trials

Commonly observed adverse reactions in 261 adult patients who received CLINOLIPID were nausea and vomiting, hyperlipidemia, hyperglycemia, hypoproteinemia, and abnormal liver function tests and occurred in 2 to 10 % of patients.

The largest clinical trial in adult patients (Study 1) enrolled 48 subjects with different underlying diagnoses. Study 2 was a randomized, open label multicenter study that enrolled 22 subjects, aged 32-81 years, who required long-term parenteral nutrition.

The most common adverse reactions in Study 1 and Study 2 were infectious complications (urinary tract infection, septicemia, and fever of unknown origin), treatment emergent abnormalities on liver/gallbladder ultrasound and abnormalities of serum chemistries, principally, hepatic function tests.

Adverse reactions reported with other intravenous lipid emulsions include hyperlipidemia, hypercoagulability, thrombophlebitis, and thrombocytopenia.

Adverse reactions reported in long-term use with other intravenous lipid emulsions include hepatomegaly, jaundice due to central lobular cholestasis, splenomegaly, thrombocytopenia, leukopenia, abnormalities in liver function tests, brown pigmentation of the liver and overloading syndrome (focal seizures, fever, leukocytosis, hepatomegaly, splenomegaly, and shock).

Pediatric Trials

The safety of CLINOLIPID in pediatric patients was evaluated in Studies 3, 4, 5, and 6 [see Clinical Studies (14.2)].

In Study 3, EFAD was defined by calculating the Holman index (the triene [Mead acid] to tetraene [arachidonic acid] ratio; T:T ratio > 0.4). Although no patient developed EFAD, one CLINOLIPID-treated patient who had a T:T ratio that increased from < 0.2 at baseline to > 0.2 at end of study treatment was considered at risk for EFAD. This patient’s arachidonic and linoleic acid levels remained within the normal range. No soybean oil lipid emulsion-treated patients had a T:T ratio ≥ 0.2.

In Studies 3, 4, 5, and 6, adverse reactions occurred at similar rates in subjects treated with CLINOLIPID and the 100% soybean oil comparator. Adverse reactions that occurred in ≥5% of patients included hyperbilirubinemia, patent ductus arteriosus, anemia, gastroesophageal reflux disease, bradycardia, feeding intolerance, neonatal intraventricular hemorrhage, increased alkaline phosphatase, atrial septal defect, hyponatremia, sepsis, and infantile apnea.

6.2 Postmarketing Experience

The following adverse reactions have been identified during use of CLINOLIPID. Because these reactions are reported voluntarily from a population of uncertain size, it is not always possible to reliably estimate their frequency or establish a causal relationship to drug exposure.

Gastrointestinal Disorders: Diarrhea

Skin and Subcutaneous Tissue Disorders: Pruritus

Immune System Disorders: Hypersensitivity reactions, including anaphylaxis [see Contraindications (4), Warnings and Precautions (5.3)]

Investigations: International normalized ratio (INR) decreased in anticoagulated patients [see Drug Interactions (7)]

Hepatobiliary disorders: cholestasis

7 DRUG INTERACTIONS

No drug interaction studies have been performed with CLINOLIPID.

Olive and soybean oils have a natural content of Vitamin K1 that may counteract the anticoagulant activity of coumadin derivatives, including warfarin.

8 USE IN SPECIFIC POPULATIONS

8.1 Pregnancy

Risk Summary

Administration of the recommended dose of CLINOLIPID is not expected to cause major defects, miscarriage, or other adverse maternal or fetal outcomes. No animal reproduction studies have been conducted with lipid injectable emulsion. There are clinical considerations if CLINOLIPID is used in pregnant women [see Clinical Considerations].

The estimated background risk of major birth defects and miscarriage for the indicated population are unknown. All pregnancies have a background risk of birth defect, loss, or other adverse outcomes. In the U.S. general population, the estimated background risk of major birth defects and miscarriage in clinically recognized pregnancies is 2 to 4% and 15 to 20%, respectively.

Clinical Considerations

Disease-Associated Maternal and/or Embryo-Fetal Risk:

Severe malnutrition in a pregnant woman is associated with preterm delivery, low birth weight, intrauterine growth restriction, congenital malformations and perinatal mortality. Parenteral nutrition should be considered if a pregnant woman’s nutritional requirements cannot be fulfilled by oral or enteral intake. It is not known whether the administration of CLINOLIPID to pregnant women provides adequate essential fatty acids to the developing fetus.

8.2 Lactation

Risk Summary

There are no data available to assess the presence of CLINOLIPID and/or its active metabolite(s) in human milk, the effects on the breastfed child or the effects on milk production. The developmental and health benefits of breastfeeding should be considered along with the mother’s clinical need for CLINOLIPID and any potential adverse effects on the breastfed child from CLINOLIPID or from the underlying maternal condition.

8.4 Pediatric Use

The safety and effectiveness of CLINOLIPID have been established as a source of calories and essential fatty acids for PN in pediatric patients, including term and preterm neonates, when oral or enteral nutrition is not possible, insufficient, or contraindicated. Use of CLINOLIPID in pediatric patients is supported by evidence from four studies that enrolled pediatric patients, including preterm and term neonates, and additional evidence from clinical studies in adults. Use of CLINOLIPID in older pediatric patients is supported by evidence from two studies in pediatric patients up to 9 years of age treated for a median of 15 and 56 days, respectively, with additional evidence from clinical studies in adults [see Clinical Studies (14.2)]. No clinically significant cases of EFAD were observed in short term pediatric clinical studies. However, one premature neonate in study 3 became at risk for EFAD after 14 days of treatment based on a Holman Index increase above 0.2. This patient’s arachidonic and linoleic acid levels remained within the normal range [see Adverse Reactions (6.1)]. Monitor pediatric patients for laboratory evidence of EFAD, including fatty acid profile (i.e., arachidonic acid) because they may be particularly vulnerable to neurologic complications if adequate amounts of essential fatty acids are not provided [see Warnings and Precautions (5.9)].

In the postmarketing setting, clinical decompensation with rapid infusion of intravenous lipid emulsion in neonates and infants, sometimes fatal, has been reported [see Warnings and Precautions (5.1)]. Because of immature renal function, preterm infants receiving prolonged treatment with CLINOLIPID may be at risk for aluminum toxicity [see Warnings and Precautions (5.8)].

8.5 Geriatric Use

Of the total number of subjects in clinical studies of CLINOLIPID, 21% were 65 and over, while 10% were 75 and over. No overall differences in safety or effectiveness were observed between these subjects and younger subjects, and other reported clinical experience has not identified differences in responses between the elderly and younger patients, but greater sensitivity of some older individuals cannot be ruled out.

10 OVERDOSAGE

In the event of overdose, serious adverse reactions may result [see Warnings and Precautions (5.1, 5.5)]. Stop the infusion to allow lipids to clear from serum. The effects are usually reversible after the lipid infusion is stopped. If medically appropriate, further intervention may be indicated. The lipid administered and fatty acids produced are not dialyzable.

11 DESCRIPTION

CLINOLIPID lipid injectable emulsion, USP is a sterile, non-pyrogenic, homogenous, white, milky lipid emulsion for intravenous infusion. The lipid content of CLINOLIPID is 0.2 g/mL and comprises a mixture of refined olive oil and refined soybean oil in an approximate ratio of 4:1 (olive:soy). The mean concentration of linoleic acid (an omega-6 essential fatty acid) is 35.8 mg/mL (range 27.6 to 44.0 mg/mL) and α-linolenic acid (an omega-3 essential fatty acid) is 4.7 mg/mL (range 1.0 to 8.4 mg/mL). The phospholipids provide 470 milligrams or 15 mmol of phosphorus per liter.

The total energy content, including fat, phospholipids and glycerin is 2000 kcal/L.

Each 100 mL of CLINOLIPID 20% contains approximately 16 g of Olive Oil NF and 4 g of Soybean Oil USP, 1.2 g Egg Phospholipids NF, 2.25 g Glycerin USP, 0.03 g Sodium Oleate, and Water for Injection USP. Sodium Hydroxide NF for pH adjustment, pH: 6.0 to 9.0.

The olive and soybean oils are refined natural products consisting of a mixture of neutral triglycerides of predominantly unsaturated fatty acids with the following structure:

The major component fatty acids are linoleic (13.8 to 22.0%), oleic (44.3 to 79.5%), palmitic (7.6 to 19.3%), linolenic (0.5 to 4.2%), palmitoleic (0.0 to 3.2%) and stearic (0.7 to 5.0%). These fatty acids have the following chemical and structural formulas:

CLINOLIPID has an osmolality of approximately 340 mOsmol/kg water (which represents an osmolarity of 260 mOsmol/liter of emulsion).

CLINOLIPID contains no more than 25 mcg/L of aluminum.

12 CLINICAL PHARMACOLOGY

CLINOLIPID administered intravenously provides biologically utilizable source of calories and essential fatty acids.

12.1 Mechanism of Action

Fatty acids serve as an important substrate for energy production. The most common mechanism of action for energy production derived from fatty acid metabolism is beta oxidation. Fatty acids are important for membrane structure and function, precursors for bioactive molecules (such as prostaglandins), and as regulators of gene expression.

12.2 Pharmacodynamics

Infused essential fatty acids are synthesized into higher derivative fatty acids. Olive oil contains significant amounts of alpha-tocopherol that contributes to Vitamin E status.

12.3 Pharmacokinetics

Metabolism and Excretion

The fatty acids, phospholipids, and glycerol found in lipid emulsions are metabolized by cells to carbon dioxide and water. The metabolism of these substances results in the generation of energy in the form of adenosine triphosphate (ATP). Some fatty acids are stored in the body in fat tissue, cell membranes, or as intracellular triglycerides. There is constant turn-over of these tissues, with the result that the lipid components are eventually metabolized to carbon dioxide and water. Carbon dioxide is expired through the lungs. Water is excreted through the kidneys or lost through evaporation/expiration through the skin, lungs, and other tissue surfaces. Some lipids (i.e., phospholipids, cholesterol, and bile acids) are excreted through the biliary system.

13 NONCLINICAL TOXICOLOGY

13.1 Carcinogenesis, Mutagenesis, Impairment of Fertility

Studies with CLINOLIPID have not been performed to evaluate the carcinogenic potential, mutagenic potential, or effects on fertility.

13.2 Animal Toxicology and/or Pharmacology

CLINOLIPID was evaluated in toxicity studies conducted in rats and dogs for up to 3 months. The principal signs of toxicity noted in the 3-month studies were:

- Slight hemolytic anemia at 12 g/kg/day in rats and at 6 g/kg/day in dogs. These doses in rats and dogs are 4 and 2 times higher, respectively, than the maximum recommended pediatric dose (3 g/kg/day) of CLINOLIPID.
- Dose-dependent decrease in urea levels in rats at 6 and 12 g/kg/day dose levels and in dogs at 3, 4.5 and 6 g/kg/day dose levels associated with decreased feed consumption.
- Hypercholesterolemia in dogs at 3, 4.5 and 6 g/kg/day dose levels.
- Hepatic pathology of lipid and pigmentary overload in male and female rats at 3, 6 and 12 g/kg/day dose levels and brownish-yellow pigmentation in vacuolated Kupffer cells in male and female dogs at 3, 4.5 and 6 g/kg/day dose levels with hepatocyte vacuolation in male dogs at 6 g/kg/day and female dogs at 4.5 and 6 g/kg/day dose levels.
- Splenic pigmentation and vacuolization in rats at 3, 6 and 12 g/kg/day dose levels, and dogs in 4.5 and 6 g/kg/day dose levels.

At doses of 3 g/kg/day, slight lipid and pigmentary overload of the liver and vacuolization of Kupffer cells were observed in rats and dogs. At a dose of 12 g/kg/day in rats, hepatocellular vacuolation, granulomatous inflammation of the liver, hepatocellular necrosis and hemosiderosis of the liver and lipid deposits and splenic hemosiderosis, were observed. In dogs, at a dose of 6 g/kg/day, brownish-yellow pigmentation in the Kupffer cells of liver and spleen, hyperplasia of vacuolated Kupffer cells, hepatocyte vacuolization, a slight increase in the number of lipid storage cells (Ito cells) in the liver and macrophage vacuolization of the spleen were observed.

14 CLINICAL STUDIES

14.1 Adult Clinical Studies

Two clinical trials (Study 1 and Study 2) in adults compared CLINOLIPID to soybean oil-based intravenous lipid emulsion. Although Study 1 and Study 2 were not adequately designed to demonstrate noninferiority of CLINOLIPID to the soybean oil comparator, they support CLINOLIPID as a source of calories and essential fatty acids in adults. The lipid dosage was variable in Studies 1 and 2 and adjusted to the patient’s nutritional requirements.

Study 1 was a randomized, open-label, multicenter study. Forty-eight patients, aged 17 to 75 years, requiring total parenteral nutrition (TPN) for ≥15 days (mean 22 days) were enrolled and randomized to either CLINOLIPID or a soybean oil-based intravenous lipid emulsion. Nutritional efficacy was assessed by anthropometric indices (body weight, arm circumference, skin-fold thickness), biomarkers of protein metabolism (total protein, albumin) and lipid metabolism. Anthropometric criteria (body weight, arm circumference, and skin fold thickness) were comparable for both groups. Mean total serum protein and albumin increased similarly in both groups.

Study 2 was a randomized, open label multicenter study that enrolled 22 patients aged 32-81 years who required long-term parenteral nutrition. Twelve patients received CLINOLIPID for a mean of 202 days (range 24 to 408 days) and 10 patients received the comparator lipid for a mean of 145 days (range 29-394 days). The two groups had similar outcomes for weight, weight loss, mid-arm circumference and triceps skinfold thickness.

14.2 Pediatric Clinical Studies

The efficacy of CLINOLIPID compared to a soybean oil-based lipid emulsions was evaluated in 179 pediatric patients in four randomized, active-controlled, parallel-group clinical studies. Three studies (161 patients) were double-blinded. Although the four pediatric clinical studies were not adequately designed to demonstrate the noninferiority of CLINOLIPID to the soybean oil comparator, they support CLINOLIPID as a source of calories and essential fatty acids in pediatric patients, including term and preterm neonates. The 179 pediatric patients (89 treated with CLINOLIPID; 90 with comparator) consisted of 140 patients who were less than 1 month of age, 23 patients one month to less than two years old, and 16 patients two to less than 18 years old. Nutritional efficacy in pediatric patients, including preterm infants, was assessed by evaluating growth parameters, protein biomarkers, changes in triglyceride and cholesterol concentrations, and fatty acid parameters.

Study 3 (NCT 04555044) randomized 102 patients (101 analyzed) to receive either CLINOLIPID (n = 50) or a soybean oil-based lipid emulsion (n = 51) as part of PN in the hospital setting. Baseline characteristics and outcomes during the study were similar in the two groups. The majority of study patients (n=94, 93%) were preterm neonates born at less than 37 weeks of gestation. The median age at enrollment in this study was day one of life and the median gestational age of neonates was 29 weeks. Eighty-five patients (84%) were very low birth weight, including 53 patients (52%) with a birth weight of 1000-1499 grams and 32 patients (32%) with a birthweight of less than 1000 g. Forty-one patients (41%) were Black, 42 (42%) were White, and 8 (8%) were Hispanic or Latino.

In both study groups, the mean daily dose administered was approximately 2.3 g/kg/day (SD 0.8 g/kg/day), and the median duration of treatment was 8 days (range: 3 – 60 days; interquartile range [IQR]: 8 – 10 days). The primary endpoint was at risk of developing EFAD, defined as triene:tetraene (T:T) ratio >0.4, which did not occur during the study in either treatment group. Secondary endpoints included incidence of parenteral nutrition-associated cholestasis (PNAC) defined as direct bilirubin ≥2 mg/dL with no other etiology identified. One patient in the CLINOLIPID group (2%) and two patients in the comparator group (3.9%) developed PNAC during the study. Median increases in body weight, length/height, and head circumference were similar between CLINOLIPID and the soybean oil comparator group.

Study 4 randomized 45 preterm neonates of which 42 were treated and analyzed for safety; 33 (n=18 on CLINOLIPID and n=15 on soybean oil lipid emulsion) completed the 7-day treatment period and were analyzed for efficacy. The study evaluated weight, fatty acid profiles, triglyceride and cholesterol levels, and protein biomarkers. Two (6%) of patients had birth weight less than 1000 grams and 14 patients (42%) weighed between 1000 and 1500 grams at birth. The mean (range) daily dose of Clinolipid was 1.5 g/kg/day (0.7 – 1.7), and median (range) treatment duration period was 7 (2 – 7) days. Complete blood counts, total bilirubin, cholesterol, triglycerides, and weight of CLINOLIPID-treated patients were similar to those treated with soybean oil lipid emulsion.

Study 5 randomized 18 pediatric patients (16 analyzed) between two and 57 months of age (median 6.3 months) who were treated with either CLINOLIPID (n = 7) or soybean oil lipid emulsion (n = 9). In both groups, the mean (SD) daily dose of lipid emulsion was 2.9 (0.4) g/kg/day and median treatment duration was 15 days (range: 1 – 29 days, IQR: 15 – 17 days). There were no meaningful differences between the groups at day 15 in weight gain, complete blood count, total bilirubin, total protein, cholesterol, or triglycerides. No patient in the study had evidence of biochemical EFAD (T:T ratio >0.4).

Study 6 evaluated the long-term safety and efficacy of CLINOLIPID in 18 pediatric patients between one and nine years of age (median, 2.5 years) who had been treated with 50% medium-chain triglycerides/50% soybean oil lipid emulsion for 30 days, and were randomized to either CLINOLIPID (n = 9) or a soybean oil lipid emulsion (n = 9) three to five days per week. Patients had received PN for a mean of 34 months prior to study entry and treatment groups had comparable fatty acid profiles, lipids, albumin, total bilirubin, and parenteral nutrition intake during the run-in period. The average daily lipid dose in the treatment period was 1.9 g/kg/day (range: 1.4 – 3 g/kg/day) in CLINOLIPID group and 1.7 g/kg/day (range: 0.9 – 2.3 g/kg/day) for the soybean oil group. The median treatment duration for CLINOLIPID was 56 days (range: 56 – 63 days; IQR: 56 – 61 days). There were no meaningful differences between treatment groups in height, weight, and albumin levels. No patient in the study had evidence of biochemical EFAD (T:T ratio > 0.4).

16 HOW SUPPLIED/STORAGE AND HANDLING

CLINOLIPID is a sterile, white, milky homogenous lipid injectable emulsion supplied in CLARITY polyolefin Flexible Containers as follows:

Strengths | Container Size | Product Code | NDC Number (1 Bag) | NDC Number (Shelf Pack)
20% (20 g/100 mL) (0.2 g/mL) | 100 mL | EADB9520 | 0338-9540-01 (single-dose Flexible Container) | 0338-9540-05 (15 pack)
20% (50 g/250 mL) (0.2 g/mL) | 250 mL | EADB9521 | 0338-9540-02 (single-dose Flexible Container) | 0338-9540-06 (10 pack)
20% (100 g/500 mL) (0.2 g/mL) | 500 mL | EADB9523 | 0338-9540-03 (single-dose Flexible Container) | 0338-9540-07 (12 pack)
20% (200 g/1,000 mL) (0.2 g/mL) | 1,000 mL | EADB9524 | 0338-9540-04 (Pharmacy Bulk Package bag) | 0338-9540-08 (6 pack)

The CLARITY Container is a lipid-compatible plastic container (PL 2401-1). The bag is packaged in an oxygen barrier overpouch, which contains an oxygen absorber / oxygen indicator sachet.

CLINOLIPID should be stored at 20°C to 25°C (68°F to 77°F). Excursion permitted between 15°C to 30 °C (59°F to 86°F). See USP Controlled Room Temperature. Protect from freezing. Avoid excessive heat. Store in overpouch until ready to use.

CLINOLIPID 100 mL, 250 mL and 500 mL single-dose Flexible Containers:
After removing the overpouch, infuse immediately. If not used immediately, the product should be stored for no longer than 24 hours at not more than 25°C (77°F) [See Dosage and Administration (2.2)].

CLINOLIPID 1,000 mL Pharmacy Bulk Package:
Use the pharmacy bulk package immediately for admixing after removal from overpouch. If not used immediately, the product should be stored for no longer than 24 hours at not more than 25°C (77°F) [see Dosage and Administration (2.2)].

17 PATIENT COUNSELING INFORMATION

When initiating CLINOLIPID administration, discuss the following information with the patient or caregiver:

Parenteral Nutrition-Associated Liver Disease and Other Hepatobiliary Disorders

Inform patients and caregivers that use of parenteral nutrition may result in parenteral nutrition-associated liver disease and/or other hepatobiliary disorders [see Warnings and Precautions (5.2)].

Hypersensitivity Reactions

Inform patients and caregivers that CLINOLIPID may cause hypersensitivity reactions, including anaphylaxis. If CLINOLIPID is infused at home, instruct patients or caregivers to stop the infusion of CLINOLIPID immediately and seek medical attention if they experience signs or symptoms of a hypersensitivity reaction, such as rapid or weak heartbeat, feeling faint, difficulty in breathing or swallowing, vomiting, nausea, headache, sweating, dizziness, hives, rash, itching, flushing dizziness, fever, or chills [see Warnings and Precautions (5.3)].

Infections

Inform patients and caregivers that patients who receive CLINOLIPID are at risk of infection. If CLINOLIPID is infused at home, instruct patients or caregivers to ensure aseptic techniques are used for the preparation and administration of CLINOLIPID and to monitor for signs and symptoms of infection [see Warnings and Precautions (5.4)].

Fat Overload Syndrome

Inform patients and caregivers that fat overload syndrome has been reported with the use of intravenous lipid emulsions. If CLINOLIPID is infused at home, instruct patients or caregivers to stop CLINOLIPID if signs or symptoms of fat overload syndrome occur [see Warnings and Precautions (5.5)].

Refeeding Syndrome

If the patient is severely malnourished, inform patients and caregivers that administering parenteral nutrition including CLINOLIPID may result in refeeding syndrome [see Warnings and Precautions (5.6)].

Hypertriglyceridemia

Inform patients and caregivers about the risks of hypertriglyceridemia with CLINOLIPID use [see Warnings and Precautions (5.7)].

Aluminum Toxicity

Inform patients and caregivers that prolonged PN administration in patients with renal impairment, including preterm neonates, may result in aluminum reaching toxic levels associated with central nervous system and bone toxicity [see Warnings and Precautions (5.8)].

Preparation and Administration Instructions

If it is acceptable for a patient or caregiver to administer CLINOLIPID at home, then provide recommendations on how to prepare, add compatible additives (when appropriate), administer, and store CLINOLIPID [see Dosage and Administration (2.1, 2.2)].

Baxter Healthcare Corporation
Deerfield, IL 60015 USA
Baxter, Clarity, Clinolipid and Exactamix are trademarks of Baxter International Inc.

PACKAGE/LABEL PRINCIPAL DISPLAY PANEL

Container Label

1000 mL

EADB9524 NDC 0338-9540-04

Baxter Logo

Clinolipid
(Lipid Injectable Emulsion, USP) 20%
200 g/1000 mL (0.2 g/mL)

Pharmacy Bulk Package
Not For Direct Infusion

Intravenous use only

1000 mL
Energy Content 2000 kcal/L

Each 100 mL contains approximately 16 g of Olive Oil NF
and 4 g of Soybean Oil USP, 1.2 g Egg Phospholipids NF,
2.25 g Glycerin USP, 0.03 g Sodium Oleate, Water for
Injection USP and Sodium Hydroxide NF for pH
adjustment pH 6.0–9.0 Osmolarity 260 mOsmol/L (calc)

Cautions Use only if the color of the oxygen indicator is
within allowable range Do not use unless emulsion has
homogeneous milky appearance

Once container closure has been penetrated
withdrawal of contents should be
completed without delay. Dispense
contents within 4 hours after initial entry.
See prescribing information for proper
use of Pharmacy Bulk Package.

Store at 20 to 25 °C (68 to 77 °F)
See USP Controlled Room Temperature
Protect from freezing
Rx Only

Bar code appears here, and is printed on line during production.

Baxter Healthcare Corporation

BE-35-04-865

EXP YYY-MM LOT

1000

750

500

250

100